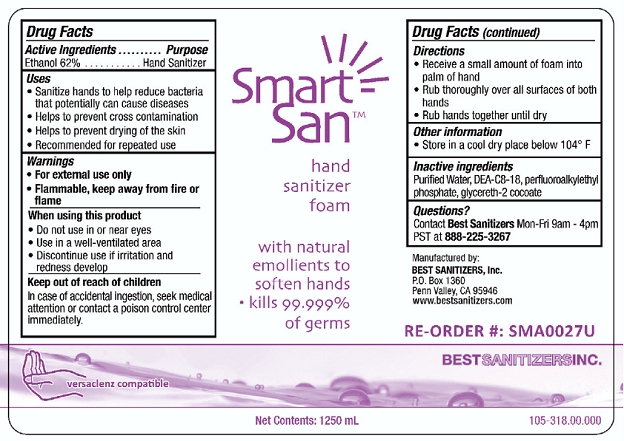 DRUG LABEL: Smart San Hand Sanitizer
NDC: 59900-117 | Form: LIQUID
Manufacturer: Best Sanitizers, Inc
Category: otc | Type: HUMAN OTC DRUG LABEL
Date: 20241205

ACTIVE INGREDIENTS: ALCOHOL 620 mL/1000 mL
INACTIVE INGREDIENTS: WATER; DIETHANOLAMINE BIS(C8-C18 PERFLUOROALKYLETHYL)PHOSPHATE; GLYCERETH-2 COCOATE

Smart San Hand Sanitizer Foam 59900-117

Active Ingredient

Ethanol 62%

Purpose

Hand Sanitizer

Uses

- Sanitize hands to help reduce bacteria that potentially can cause disease
- Helps to prevent cross contamination
- Helps to prevent drying of the skin
- Recommended for repeated use

Warnings

- For external use only
- Flammable, keep away from fire or flame

When using this product

- Do not use in or near eyes
- Use in a well-ventilated area
- Discontinue use if irritation and redness develop

Keep out of reach of children

In case of accidental ingestion, seek medical attention or contact a poison control center immediately.

Directions

- Receive a small amount of foam into palm of hand
- Rub thoroughly over all surfaces of both hands
- Rub hands together until dry

Other Information

Store in a cool dry place below 104° F

Inactive ingredients

purified water, DEA-C8-18, perfluomalkylethyl phosphate, glycereth-2 cocoate

Questions?

Contact Best SanitizersMon-Fri 9am - 4pm PST at 888-225-3267

PACKAGE LABEL

NDC 59900--117-02

NDC 59900--117-03

NDC 59900--117-04

NDC 59900--117-05

NDC 59900--117-06

NDC 59900--117-07

NDC 59900--117-08

Smart San™ Hand Sanitizer Foam